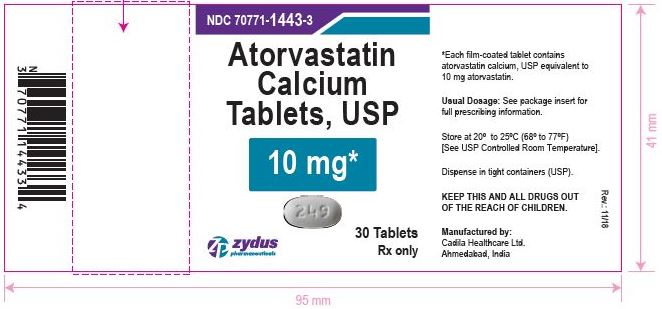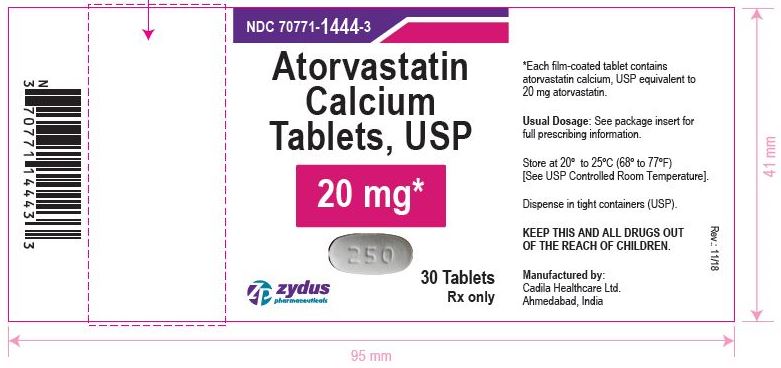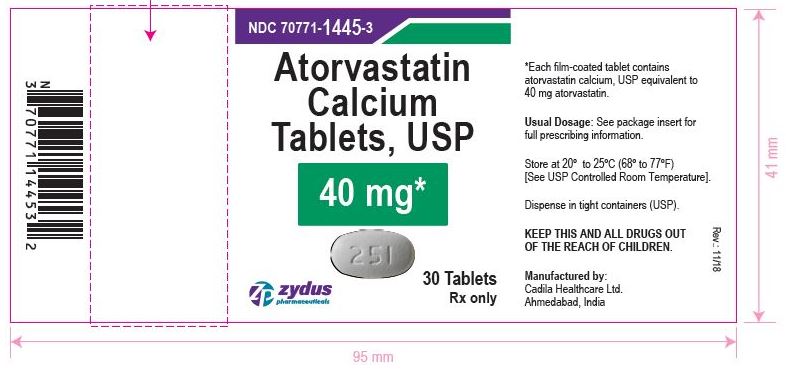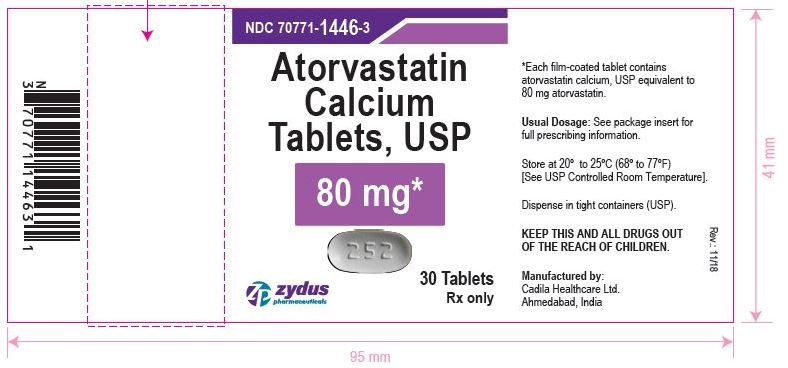 DRUG LABEL: atorvastatin calcium
NDC: 70771-1443 | Form: TABLET
Manufacturer: Zydus Lifesciences Limited
Category: prescription | Type: HUMAN PRESCRIPTION DRUG LABEL
Date: 20241021

ACTIVE INGREDIENTS: ATORVASTATIN CALCIUM TRIHYDRATE 10 mg/1 1
INACTIVE INGREDIENTS: CALCIUM CARBONATE; CROSCARMELLOSE SODIUM; HYDROXYPROPYL CELLULOSE (110000 WAMW); HYPROMELLOSES; LACTOSE MONOHYDRATE; MAGNESIUM STEARATE; CELLULOSE, MICROCRYSTALLINE; POLYETHYLENE GLYCOL, UNSPECIFIED; POLYSORBATE 80; TITANIUM DIOXIDE; TALC

ATORVASTATIN CALCIUM TABLETS.

PACKAGE LABEL

NDC 70771-1443-3

Atorvastatin Calcium Tablets, USP 10 mg

Rx Only

30 Tablets

NDC 70771-1444-3

Atorvastatin Calcium Tablets, USP 20 mg

Rx Only

30 Tablets

NDC 70771-1445-3

Atorvastatin Calcium Tablets, USP 40 mg

Rx Only

30 Tablets

NDC 70771-1446-3

Atorvastatin Calcium Tablets, USP 80 mg

Rx Only

30 Tablets